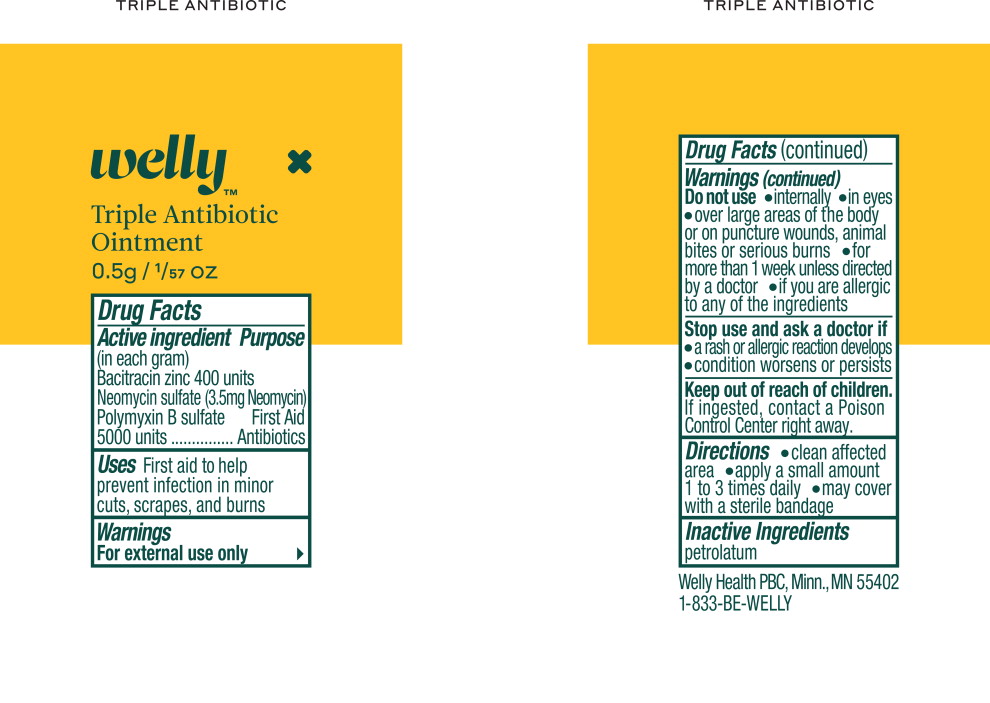 DRUG LABEL: Antibiotic
NDC: 72663-560 | Form: OINTMENT
Manufacturer: Welly Health PBC
Category: otc | Type: HUMAN OTC DRUG LABEL
Date: 20250129

ACTIVE INGREDIENTS: BACITRACIN ZINC 6 mg/1 mL; NEOMYCIN SULFATE 3.5 mg/1 mL; POLYMYXIN B SULFATE 0.77 mg/1 mL
INACTIVE INGREDIENTS: PETROLATUM

Drug Facts

Active ingredient

(in each gram)

Bacitracin zinc 400 units

Neomycin sulfate (3.5 mg Neomycin) Polymyxin B sulfate 5000 units

Purpose

First Aid

Antibiotics

Uses

First aid to help prevent infection in minor cuts, scrapes, and burns

Warnings

External use only.

Do not use

- internally
- in eyes
- over large areas of the body or on puncture wounds, animal bites or serious burns
- for more than 1 week unless directed by a doctor
- if you are allergic to any of the ingredients

Stop use, ask a doctor

- a rash or allergic reactions develops
- condition worsens or persists

Keep out of reach of children.

If ingested, contact a Poison Control Center right away.

Directions

- clean affected area
- apply a small amount 1 to 3 times daily
- may cover with a sterile bandage

Inactive ingredients

petrolatum

Welly Health PBC, Minn., MN 55402

1-833-BE-WELLY

Principal Display Panel - Antibiotic Pouch Label

Welly™

Triple Antibiotic
Ointment

0.5g/ 1/57 OZ